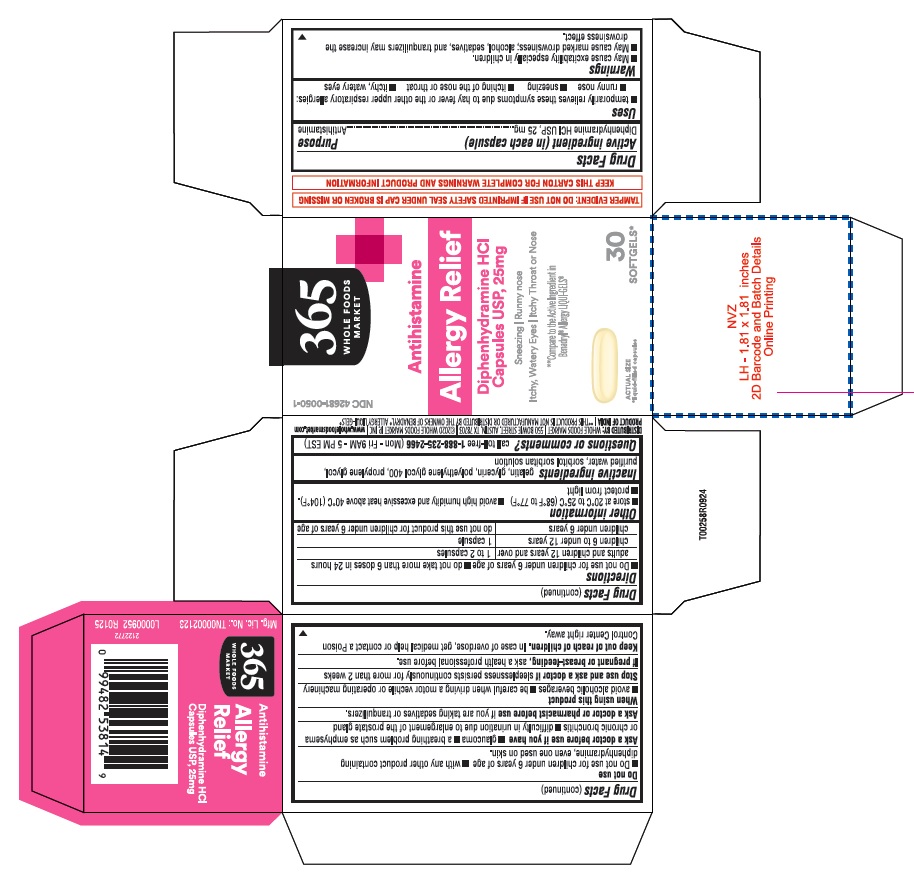 DRUG LABEL: Allergy Relief
NDC: 42681-0050 | Form: CAPSULE, LIQUID FILLED
Manufacturer: Whole Foods Market, INC.
Category: otc | Type: HUMAN OTC DRUG LABEL
Date: 20251201

ACTIVE INGREDIENTS: DIPHENHYDRAMINE HYDROCHLORIDE 25 mg/1 1
INACTIVE INGREDIENTS: SORBITAN; GELATIN; POLYETHYLENE GLYCOL 400; WATER; GLYCERIN; PROPYLENE GLYCOL; SORBITOL

Whole foods-Diphenhydramine Hydrochloride capsules, 25 mg-dye free

Active ingredient (in each capsule)

Diphenhydramine HCl 25 mg

Purpose

Antihistamine

Uses

■ temporarily relieves these symptoms due to hay fever or the other upper respiratory allergies:
■ runny nose ■ sneezing ■ itching of the nose or throat ■ itchy, watery eyes

Warnings

■ May cause excitability especially in children.
■ May cause marked drowsiness; alcohol, sedatives, and tranquilizers may increase the drowsiness effect.

■ Do not use for children under 6 years of age ■ with any other product containing diphenhydramine, even one used on skin.

Ask a doctor before use if you have

■ glaucoma ■ a breathing problem such as emphysema or chronic bronchitis ■ difficulty in urination due to enlargement of the prostate gland

Ask a doctor or pharmacist before use

if you are taking sedatives or tranquilizers.

When using this product

■ avoid alcoholic beverages ■ be careful when driving a motor vehicle or operating machinery

Stop use and ask a doctor if

sleeplessness persists continuously for more than 2 weeks

If pregnant or breast-feeding,

ask a health professional before use.

Keep out of reach of children.

In case of overdose, get medical help or contact a Poison Control Center right away.

Directions

■ Do not use for children under 6 years of age ■ do not take more than 6 doses in 24 hours

adults and children 12 years and over | 1 to 2 capsules
children 6 to under 12 years | 1 capsule
children under 6 years | do not use this product for children under 6 years of age

Other information

■ store at 20°C to 25°C (68°F to 77°F)
■ avoid high humidity and excessive heat above 40°C (104°F).
■ protect from light

Inactive ingredients

gelatin, glycerin, polyethylene glycol 400, propylene glycol, purified water, sorbitol sorbitan solution

Questions or comments?

call toll-free 1-888-235-2466(Mon - Fri 9AM - 5PM EST)

TAMPER EVIDENT: DO NOT USE IF IMPRINTED SAFETY SEAL UNDER CAP JS BROKEN OR MISSING

KEEP THIS CARTON FOR COMPLETE WARNINGS AND PRODUCT INFORMATION

DISTRIBUTED BY: WHOLE FOODS MARKET | 550 BOWIE STREET, AUSTIN, TX 78703 |©2020 WHOLE FOODS MARKET IP, INC | www.wholefoodsmarket.com

PRODUCT OF INDIA| ** THIS PRODUCT IS NOT MANUFACTURED OR DISTRIBUTED BY THE OWNERS OF BENADRYL®ALLERGY LIQUI-GELS®

Mfg.Lic. No. : TN00002123

2122772

L0000952

R0125

30's count

NDC 42681-0050-1

365

WHOLE FOODS MARKET

Antihistamine

Allergy Relief

Diphenhydramine HCl

Capsules USP, 25 mg

Sneezing | Runny nose

Itchy, Watery Eyes | Itchy Throat or Nose

** Compare to the Active Ingridient in

Benadryl®Allergy LIQUI-GELS®

30

SOFTGELS*

*liquid-filled capsules